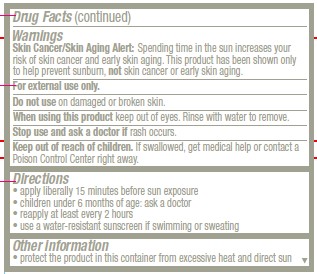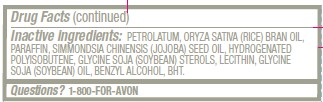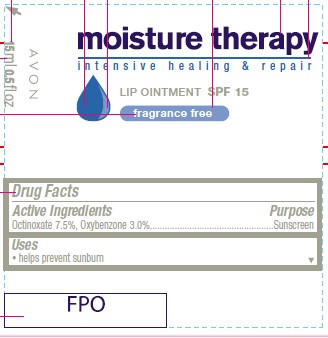 DRUG LABEL: moisture therapy
NDC: 10096-0103 | Form: OINTMENT
Manufacturer: New Avon LLC
Category: otc | Type: HUMAN OTC DRUG LABEL
Date: 20160211

ACTIVE INGREDIENTS: OCTINOXATE	 75 mg/1 mL; OXYBENZONE 30 mg/1 mL

Active Ingredients
Octinoxate 7.5%, Oxybenzone 3.0%..............

Purpose
................ Sunscreen

Uses
■ helps prevent sunburn

WARNINGS
Skin Cancer/Skin Aging Alert: Spending time in the sun increases your risk of skin cancer and early skin aging. This product has been shown only to help prevent sunburn, not skin cancer or early skin aging.

For external use only

Do not use on damaged or broken skin

When using this product keep out of eyes. Rinse with water to remove.

Stop use and ask a doctor if rash occurs

Keep out of reach of children. If swallowed, get medical help or
contact a Poison Control Center right away.

Directions
• apply liberally 15 minutes before sun exposure
• children under 6 months of age: ask a doctor
• reapply at least every 2 hours
• use a water-resistant sunscreen if swimming or sweating

Other Information
■ protect the product in this container from excessive heat and direct sun.

INACTIVE INGREDIENT

Inactive ingredients: PETROLATUM, ORYZA SATIVA (RICE) BRAN OIL, PARAFFIN, SIMMONDSIA CHINENSIS (JOJOBA) SEED OIL, HYDROGENATED POLYISOBUTENE, GLYCINE SOJA (SOYBEAN) STEROLS, LECITHIN, GLYCINE SOJA (SOYBEAN) OIL, BENZYL ALCOHOL, BHT.

Questions? 1-800-FOR-AVON